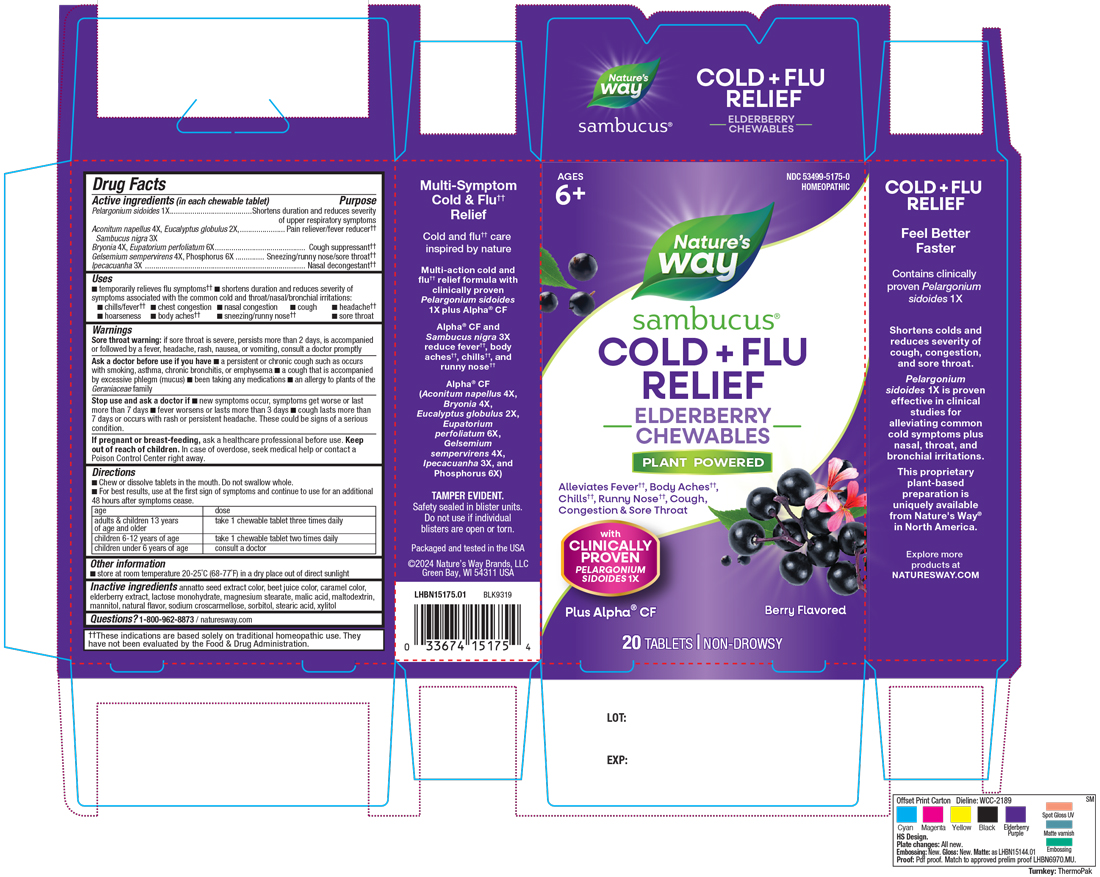 DRUG LABEL: Sambucus Cold Flu Relief Elderberry
NDC: 53499-5175 | Form: TABLET, CHEWABLE
Manufacturer: Schwabe North America, Inc.
Category: homeopathic | Type: HUMAN OTC DRUG LABEL
Date: 20251022

ACTIVE INGREDIENTS: PELARGONIUM SIDOIDES ROOT 1 [hp_X]/1 1; ACONITUM NAPELLUS 4 [hp_X]/1 1; BRYONIA ALBA ROOT 4 [hp_X]/1 1; EUCALYPTUS GLOBULUS LEAF 2 [hp_X]/1 1; SAMBUCUS NIGRA FLOWERING TOP 3 [hp_X]/1 1; EUPATORIUM PERFOLIATUM FLOWERING TOP 6 [hp_X]/1 1; GELSEMIUM SEMPERVIRENS ROOT 4 [hp_X]/1 1; IPECAC 3 [hp_X]/1 1; PHOSPHORUS 6 [hp_X]/1 1
INACTIVE INGREDIENTS: ANNATTO; BEET JUICE; CARAMEL; EUROPEAN ELDERBERRY; LACTOSE MONOHYDRATE; MAGNESIUM STEARATE; MALIC ACID; MALTODEXTRIN; MANNITOL; CROSCARMELLOSE SODIUM; SORBITOL; STEARIC ACID; XYLITOL

Sambucus Cold Flu Relief Elderberry Chewable Tablet

Active Ingredient

Pelargonium sidoides 1X

Aconitum napellus 4X

Eucalyptus globulus 2X

Sambucus nigra 3X

Bryonia 4X

Eupatorium perfoliatum 6X

Gelsemium sempervirens 4X

Phosphorus 6X

Ipecacuanha 3X

Inactive Ingredient

Annatto Seed Extract Color

Beet Juice Color

Caramel Color

Elderberry Extract

Lactose Monohydrate

Magnesium Stearate

Malic Acid

Maltodextrin

Mannitol

Natural Flavor

Sodium Croscarmellose

Sorbitol

Stearic Acid

Xylitol

Indications & Usage

Temporarily relieves flu symptoms.

Shortens duration and reduces severity of symptoms associated with the common cold and throat/nasal/bronchial irritations: chills/fever, chest congestion, nasal congestion, cough, headache, hoarseness, body aches, sneezing/runny nose, sore throat.

Purpose

Temporarily relieves flu symptoms.

Shortens duration and reduces severity of symptoms associated with the common cold and throat/nasal/bronchial irritations: chills/fever, chest congestion, nasal congestion, cough, headache, hoarseness, body aches, sneezing/runny nose, sore throat.

Dosage and Administration

Directions

Chew or dissolve tablets in the mouth. Do not swallow whole.

For best results, use at the first sign of symptoms and continue to use for an additional 48 hours after symptoms cease.
Adults and children 13 years of age and older: Take 1 chewable tablet three times daily.

Children 6-12 years of age: Take 1 chewable tablet two times daily.

Children under 6 years of age: Consult a doctor.

Warnings

Sore throat warning: if sore throat is severe, persists more than 2 days, is accompanied or followed by a fever, headache, rash, nausea, or vomiting, consult a doctor promptly.

Ask Doctor

Ask a doctor before use if you have a persistent or chronic cough such as occurs with smoking, asthma, chronic bronchitis, or emphysema, a cough that is accompanied by excessive phlegm (mucus), been taking any medications, an allergy to plants of the Geraniaceae family.

Stop Use

Stop use and ask a doctor if new symptoms occur, symptoms get worse or last more than 7 days, fever worsens or lasts more than 3 days, cough lasts more than 7 days or occurs with rash or persistent headache.

These could be signs of a serious condition.

Pregnancy or breast feeding

If you are pregnant or breast-feeding, ask a healthcare professional before use.

Keep out of reach of children

Overdose

In case of overdose, seek medical help or contact a Poison Control Center right away.